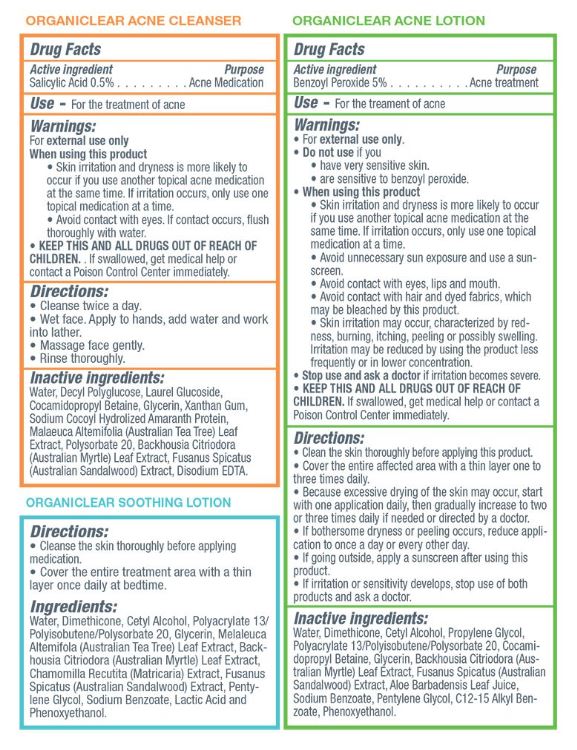 DRUG LABEL: 30 day Acne Treatment Kit
NDC: 56152-0250 | Form: KIT | Route: TOPICAL
Manufacturer: Cosmetic Enterprises Ltd
Category: otc | Type: HUMAN OTC DRUG LABEL
Date: 20251010

ACTIVE INGREDIENTS: BENZOYL PEROXIDE 5 g/100 mL; SALICYLIC ACID 0.5 g/100 mL
INACTIVE INGREDIENTS: WATER; DIMETHICONE; BACKHOUSIA CITRIODORA LEAF; PENTYLENE GLYCOL; GLYCERIN; ALOE VERA LEAF; SODIUM BENZOATE; COCAMIDOPROPYL BETAINE; CETYL ALCOHOL; SANTALUM SPICATUM WHOLE; GLYCERIN; COCAMIDOPROPYL BETAINE; XANTHAN GUM; BACKHOUSIA CITRIODORA LEAF; EDETATE DISODIUM ANHYDROUS; WATER; MELALEUCA ALTERNIFOLIA LEAF; SANTALUM SPICATUM WHOLE; POLYSORBATE 20

30 day Acne Treatment Kit

Acne Cleanser

Active ingredients Purpose

Salicylic Acid 0.5% Acne Medication

Acne Lotion

Active Ingredient Purpose

Benzoyl Peroxide 5% Acne treatment

PURPOSE

Use- For the Treatment of acne

KEEP OUT OF REACH OF CHILDREN

Keep this and all drugs out of reach of children.If swallowed, get medical help or contact a Poison Control Center immdiately.

Stop use and ask a doctorif irritation becomes severe.

Acne Cleanser

Warnings:

For external use only

when using this product

- Skin irritation and dryness is more likely to occur if you use another topical acne medication at the same time. If irritation occurs, only use one topical medication at a time.
- Avoid contact with eyes, If contact occurs, flush thoroughly with water.

Acne Lotion

Warnings:

- For external use only
- Do not useif you
- have very sensitive skin
- are sensitive to benzoyl peroxide.
- When using this product
- Skin irritation and dryness is more likely to occur if you use another topical acne medication at the same time. If irritation occurs, only use one topical medication at a time
- Avoid unnecess sun exposure and use a sunscreen
- Avoid contact with eyes, lips and mouth
- Avoid contact with hair and dyed fabrics, which may be bleached by this product
- Skin irritation may occur, characterized by redness, burning, itching, peeling, or possibly swelling. Irritation may be reduced by using the product less frequently or in lower concentration.

Acne Cleanser

Directions:

- Cleanse twice a day.
- Wet face. Apply to hands, add water and work into lather.
- Massage Face gently.
- Rinse thoroughly.

Acne Lotion

Directions:

- Clean the skin thoroughly before applying this product.
- Cover the entire affected area with a thin layer one to three times daily.
- Because excessive drying of the skin may occur, start with one application daily, then gradually increase to two or three times daily if needed or directed by a doctor
- If bothersome dryness or peeling occurs, reduce application to once a day or every other day
- If going outside, apply a sunscreen after using this product
- If irritation or sensitivity develops, stop use of both products and ask a doctor

Acne Cleanser

Inactive ingredients:

Water, Decyl Polyglucose, Laurel Glucoside, Cocamidopropyl Betaine, Glycerin, Xanthan Gum, Sodium Cocoyl Hydrolized Amaranth Protein, Malaleuca Alternifolia (Australian Tea Tree) Leaf Extract, Polysorbate 20, Backhousia Citriodora (Australian Myrtle) Leaf Extract, Fusanus Spicatus (Australian Sandalwood) Extract, Disodium EDTA.

Acne Lotion

Inactive Ingredients:

Water, Dimethicone,Cetyl Alcohol, Propylene Glycol, Polyacrylate 13/polyisobutene/ Polysorbate 20, Cocamidopropyl Betaine, Glycerin, Backhouseia Citriodora (Australian Myrtle) Leaf Extract, Fusanus Spicatus (Australian Sandalwood) Extract, Aloe Barbadensis Leaf Juice, Sodium Benzoate, Pentylene Glycol, C12-15 Alkyl Benzoate, Phenoxyethanol.

PACKAGE LABEL

Organiclear Acne Kit